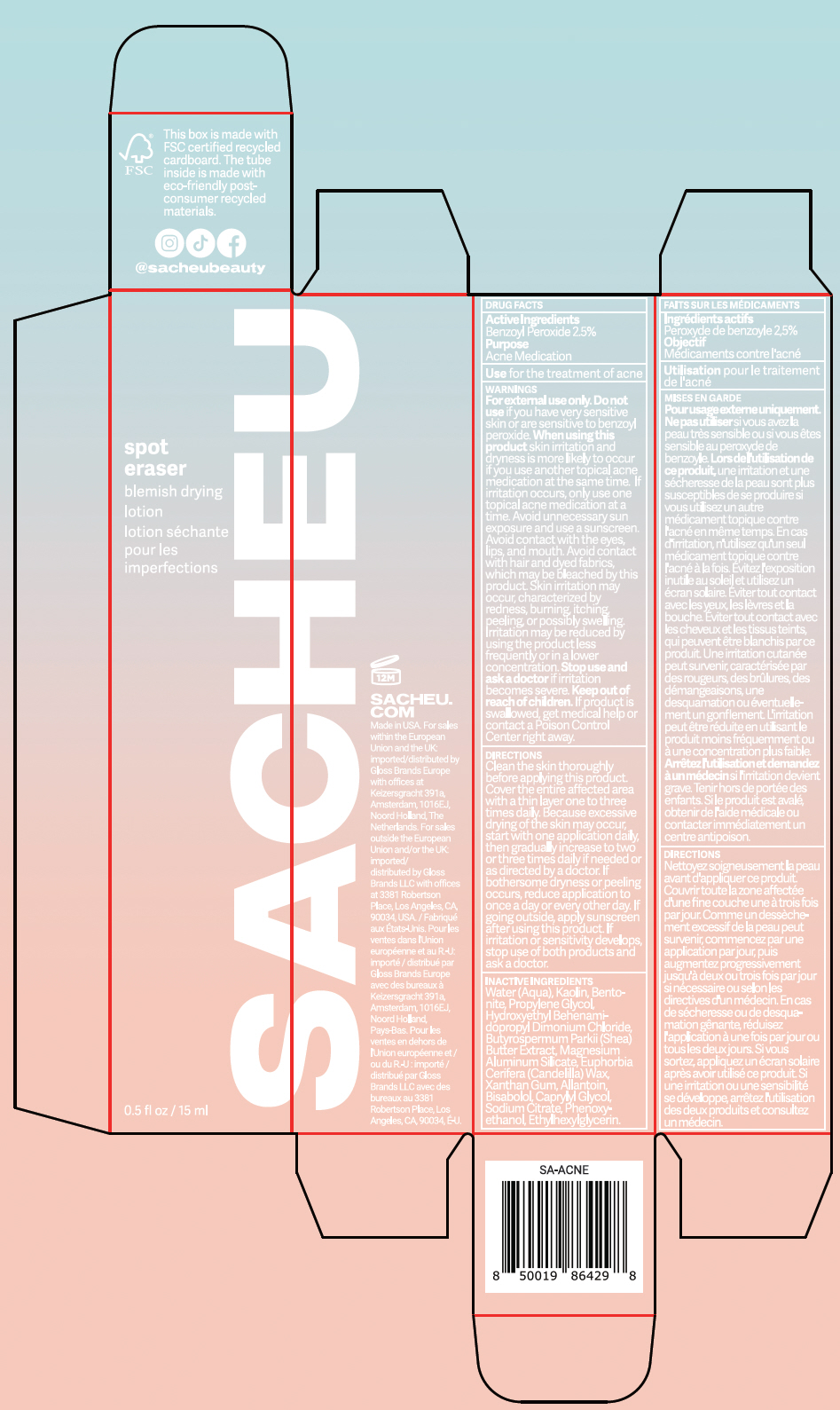 DRUG LABEL: Sacheu Spot Eraser
NDC: 83101-004 | Form: LOTION
Manufacturer: Sacheu Beauty Inc.
Category: otc | Type: HUMAN OTC DRUG LABEL
Date: 20221205

ACTIVE INGREDIENTS: BENZOYL PEROXIDE 2.5 g/100 mL
INACTIVE INGREDIENTS: WATER 65.0188 g/100 mL; KAOLIN 19 g/100 mL; BENTONITE 6 g/100 mL; PROPYLENE GLYCOL 3 g/100 mL; HYDROXYETHYL BEHENAMIDOPROPYL DIMONIUM CHLORIDE 1.32 g/100 mL; SHEA BUTTER 0.88 g/100 mL; MAGNESIUM ALUMINUM SILICATE 0.6 g/100 mL; CANDELILLA WAX 0.55 g/100 mL; XANTHAN GUM 0.13 g/100 mL; ALLANTOIN 0.0003 g/100 mL; LEVOMENOL 0.0003 g/100 mL; CAPRYLYL GLYCOL 0.0003 g/100 mL; SODIUM CITRATE, UNSPECIFIED FORM 0.0003 g/100 mL; PHENOXYETHANOL 0.86 g/100 mL; ETHYLHEXYLGLYCERIN 0.14 g/100 mL

Sacheu Spot Eraser

Drug Facts

Active Ingredients

Benzoyl Peroxide (2.5%)

Purpose

Acne Medication

Uses

- For the treatment of acne

Warnings

DO NOT USE

For external use only. Do not use if you have very sensitive skin or are sensitive to benzoyl peroxide.

When using this product skin irritation and dryness is more likely to occur if you use another topical acne medication at the same time. If irritation occurs, only use one topical acne medication at a time. Avoid unnecessary sun exposure and use a sunscreen. Avoid contact with the eyes, lips, and mouth. Avoid contact with hair and dyed fabrics, which may be bleached by this product. Skin irritation may occur, characterized by redness, burning, itching, peeling, or possibly swelling. Irritation may be reduced by using the product less frequently or in a lower concentration.

Stop use and ask a doctor if irritation becomes severe.

Keep out of reach of children. If product is swallowed, get medical help or contact a Poison Control Center right away.

Directions

- Clean the skin thoroughly before applying this product
- Cover the entire affected area with a thin layer one to three times daily. Because excessive drying of the skin may occur, start with on application daily, then gradually increase to two or three times daily if needed or as directed by a doctor. If bothersome dryness or peeling occurs, reduce application to once a day or every other day.
- If going outside, apply sunscreen after using this product. If irritation or sensitivity develops, stop use of both products and ask a doctor.

Inactive Ingredients

Water (Aqua), Kaolin, Bentonite, Propylene Glycol, Hydroxyethyl Behenamidopropyl Dimonium Chloride, Butyrospermum Parkii (Shea) Butter Extract, Magnesium Aluminum Silicate, Euphorbia Cerifera (Candelilla) Wax, Xanthan Gum, Allantoin, Bisabolol, Caprylyl Glycol, Sodium Citrate, Phenoxyethanol, Ethylhexylglycerin.

imported/distributed by
Gloss Brands Europe
with offices at
Keizersgracht 391a,
Amsterdam, 1016EJ,
Noord Holland, The
Netherlands.

imported/
distributed by Gloss
Brands LLC with offices
at 3381 Robertson
Place, Los Angeles, CA,
90034, USA.

PRINCIPAL DISPLAY PANEL - 15 ml Tube Carton

spot
eraser

blemish drying
lotion

0.5 fl oz / 15 ml

SACHEU